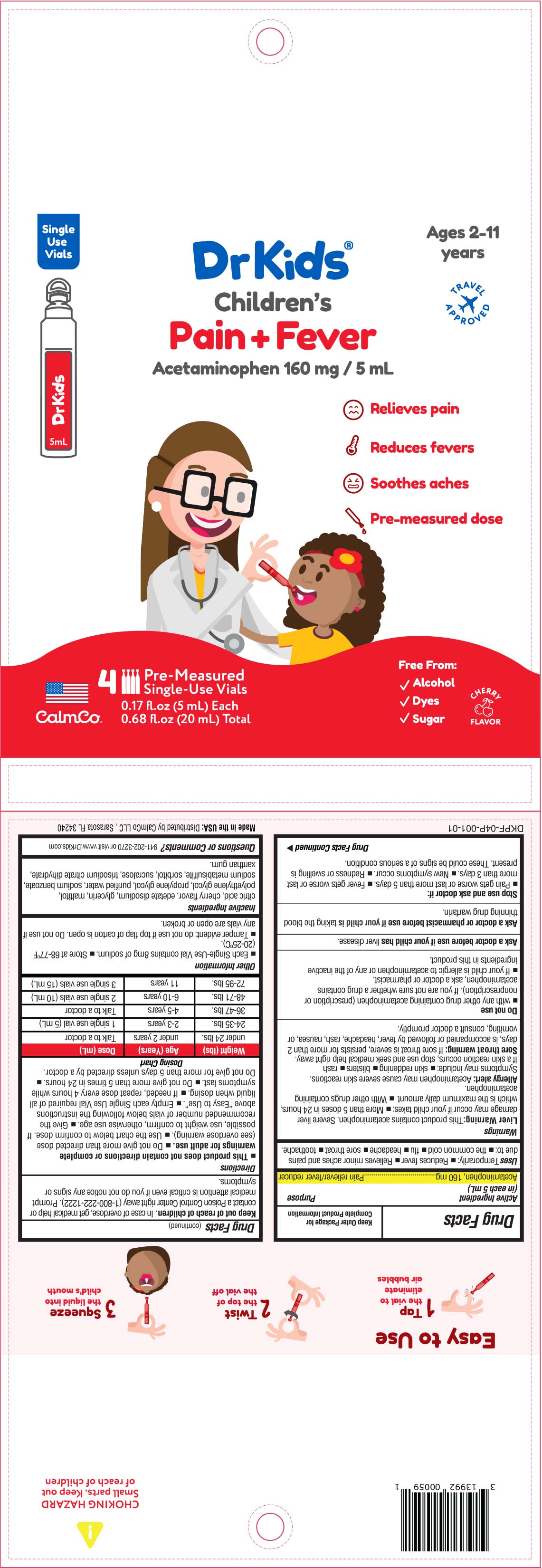 DRUG LABEL: Childrens Pain and Fever
NDC: 73282-2164 | Form: SOLUTION
Manufacturer: CalmCo LLC
Category: otc | Type: HUMAN OTC DRUG LABEL
Date: 20230724

ACTIVE INGREDIENTS: ACETAMINOPHEN 160 mg/5 mL
INACTIVE INGREDIENTS: SODIUM METABISULFITE; WATER; TRISODIUM CITRATE DIHYDRATE; GLYCERIN; PROPYLENE GLYCOL; POLYETHYLENE GLYCOL, UNSPECIFIED; SUCRALOSE; SORBITOL; CITRIC ACID MONOHYDRATE; MALTITOL; EDETATE DISODIUM; SODIUM BENZOATE; XANTHAN GUM

DrKids Children's Pain and Fever

Active Ingredient (in each 5mL)

Acetaminophen, 160mg

Purpose

Pain reliever/fever reducer

Uses

Temporarily: • reduces fever
• relieves minor aches and pains due to: • the common cold • flu • headache • sore throat • toothache

Warnings

Liver Warning: This product contains acetaminophen. Severe liver damage may occur if your child takes • more than 5 doses in 24 hours, which is the maximum daily amount for this product • With other drugs containing acetaminophen

Allergy alert: acetaminophen may cause severe skin reactions. Symptoms may include: • skin reddening • blisters • rash. If a skin reaction occurs, stop use and seek medical help right away.

Sore throat warning: If sore throat is severe, persists for more than 2 days, is accompanied or followed by fever, headache, rash, nausea, or vomiting consult a doctor promptly.

Ask a doctor before use if your child has liver disease

Ask a doctor or pharmacist before use if your child is taking the blood thinning drug warfarin.

Stop use and ask a doctor if
• pain gets worse or lasts more than 5 days
• fever gets worse or lasts more than 3 days
• new symptoms occur
• redness or swelling is present. These could be signs of a serious condition.

Keep out of reach of children

In case of overdose, get medical help or contact a Poison Control Center right away (1-800-222-1222). Prompt medical attention is critical even if you do not notice any signs or symptoms.

Do not use

• with any other drug containing acetaminophen (prescription or nonprescription). If you are not sure whether a drug contains acetaminophen, ask a doctor or pharmacist

• If your child is allergic to acetaminophen or any of the inactive ingredients in this product

Directions

• this product does not contain directions or complete warnings for adult use.
• do not give more than directed (see overdose warning)
• use the chart below to confirm dose. If possible, use weight to confirm, otherwise use age
• give the recommended number of vials below following the instructions under "Easy to Use" on the side panel.
• empty each Single-Use Vial required of all liquid when dosing
• if needed, repeat dose every 4 hours while symptoms last
• do not give more than 5 times in 24 hours
• do not give for more than 5 days unless directed by a doctor

Dosing Chart

Weight (lbs) | Age (Years) | Dose (mL)
under 24 lbs | under 2 years | Talk to a doctor
24 -35 lbs | 2 - 3 years | 1 Single-Use Vial (5 mL)
36 - 47 lbs | 4-5 years | Talk to a doctor
48 - 71 lbs | 6-10 years | 2 Single-Use Vial (10 mL)
72 - 95 lbs | 11 years | 3 Single-Use Vial (15 mL)

Other information

- each Single-Use vial contains 8mg of sodium
- store at 68-77ºF (20-25ºC)
- tamper evident: do not use if top flap of carton is open. Do not use if any vials are open or broken

Inactive ingredients

citric acid, cherry flavor, edetate disodium, glycerin, maltitol, polyethylene glycol, propylene glycol, purified water, sodium benzoate, sodium metabisulfite, sorbitol, sucralose, trisodium citrate dihydrate, xanthan gum

Questions or Comments?

+1 941-202-3270 or visit www.DrKids.com